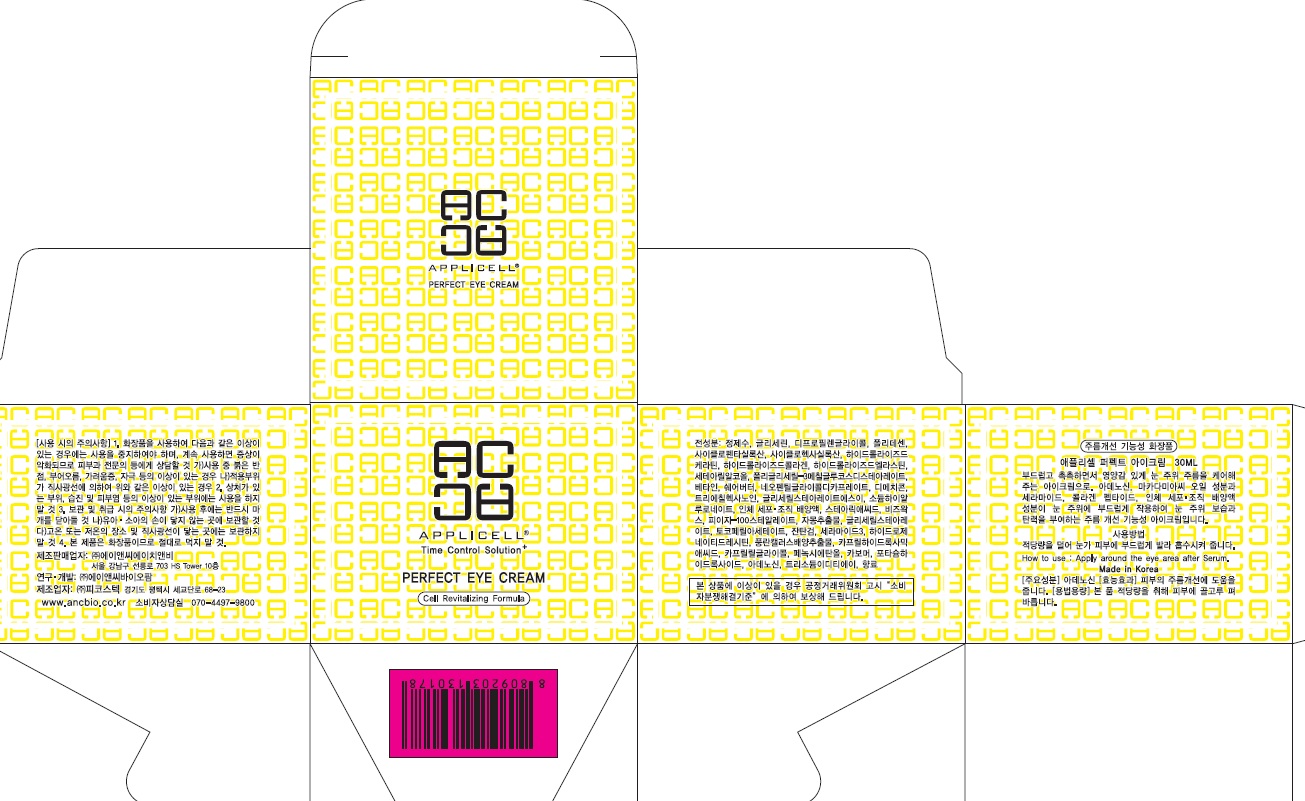 DRUG LABEL: Applicell Perfect Eye
NDC: 71098-050 | Form: CREAM
Manufacturer: Anc HnB Inc.
Category: otc | Type: HUMAN OTC DRUG LABEL
Date: 20161125

ACTIVE INGREDIENTS: Adenosine 0.01 g/30 mL
INACTIVE INGREDIENTS: Water; Glycerin

ACTIVE INGREDIENT

Active Ingredient: Adenosine 0.04%

INACTIVE INGREDIENT

Inactive Ingredients: Water, Glycerin, Dipropylene Glycol, Hydrogenated Polydecene, Cyclopentasiloxane, Cyclohexasiloxane, Hydrolyzed Keratin, Hydrolyzed Collagen, Hydrolyzed Elastin, Cetearyl Alcohol, Polyglyceryl-3 Methylglucose Distearate, Betaine, Butyrospermum Parkii(Shea Butter), Neopentyl Glycol Dicaprate, Dimethicone, Triethylhexanoin, Glyceryl Stearate SE, Sodium Hyaluronate, Human fibroblast Conditioned Media, Stearic Acid, Beeswax, PEG-100 Stearate, Citrus Paradisi (Grapefruit) Fruit Extract, Glyceryl Stearate, Tocopheryl Acetate, Xanthan Gum, Ceramide 3, Hydrogenated Lecithin, Neofinetia Falcata Callus Culture Extract, Caprylhydroxamic Acid, Caprylyl Glycol, Phenoxyethanol, Carbomer, Potassium Hydroxide, Trisodium EDTA, Fragrance

PURPOSE

Purpose: Skin Protectant

WARNINGS

Warnings: For external use only When using this product do not get into eyes, Stop use and ask a doctor if rash occurs Do not use on - deep puncture wounds - animal bites - serious burns Keep out of reach of children

KEEP OUT OF REACH OF CHILDREN

INDICATIONS & USAGE

Indications & usage: APPLICELL Perfect Eye Cream will moist and elastically care for wrinkle around the eyes.

DOSAGE & ADMINISTRATION

How to use: Apply around the eye area after Serum